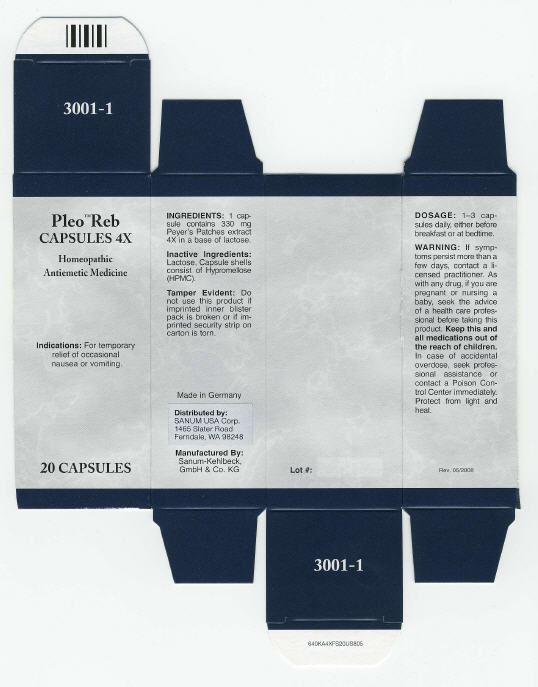 DRUG LABEL: Pleo Reb
NDC: 60681-3001 | Form: CAPSULE
Manufacturer: Sanum Kehlbeck GmbH & Co. KG
Category: homeopathic | Type: HUMAN OTC DRUG LABEL
Date: 20100106

ACTIVE INGREDIENTS: sus scrofa small intestine mucosa lymph follicle 4 [hp_X]/1 1
INACTIVE INGREDIENTS: lactose; hypromellose

Pleo™ Reb
CAPSULES 4X

Homeopathic Antiemetic Medicine

20 CAPSULES

Indications

For temporary relief of occasional nausea or vomiting.

INGREDIENTS

1 capsule contains 330 mg Peyer's Patches extract 4X in a base of lactose.

Inactive Ingredients

Lactose, Capsule shells consist of Hypromellose (HPMC).

Tamper Evident

Do not use this product if imprinted inner blister pack is broken or if imprinted security strip on carton is torn.

DOSAGE

1–3 capsules daily, either before breakfast or at bedtime.

WARNING

If symptoms persist more than a few days, contact a licensed practitioner. As with any drug, if you are pregnant or nursing a baby, seek the advice of a health care professional before taking this product.

KEEP OUT OF REACH OF CHILDREN

Keep this and all medications out of the reach of children. In case of accidental overdose, seek professional assistance or contact a Poison Control Center immediately.

STORAGE AND HANDLING

Protect from light and heat.

Made in Germany

Distributed by:
SANUM USA Corp.
1465 Slater Road
Ferndale, WA 98248

Manufactured By:
Sanum-Kehlbeck,
GmbH & Co. KG

Rev. 05/2008

PRINCIPAL DISPLAY PANEL - 20 Capsule Carton

Pleo™ Reb
CAPSULES 4X

Homeopathic
Antiemetic Medicine

Indications: For temporary
relief of occasional
nausea or vomiting.

20 CAPSULES